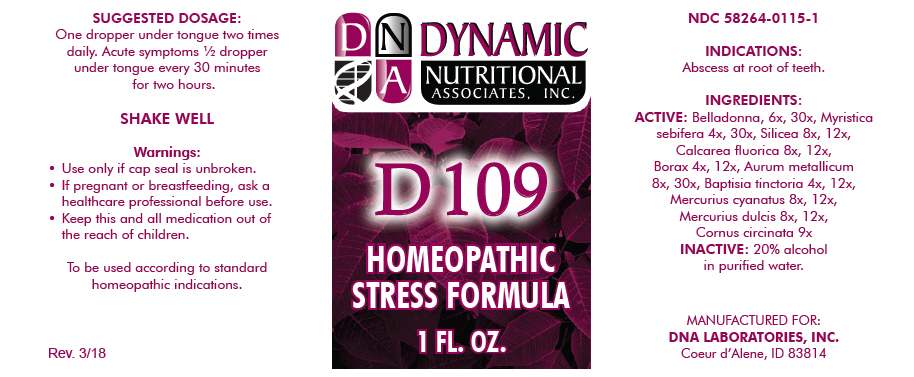 DRUG LABEL: D-109
NDC: 58264-0115 | Form: SOLUTION
Manufacturer: DNA Labs, Inc.
Category: homeopathic | Type: HUMAN OTC DRUG LABEL
Date: 20250113

ACTIVE INGREDIENTS: ATROPA BELLADONNA 6 [hp_X]/1 mL; VIROLA SEBIFERA RESIN 4 [hp_X]/1 mL; SILICON DIOXIDE 8 [hp_X]/1 mL; CALCIUM FLUORIDE 8 [hp_X]/1 mL; SODIUM BORATE 4 [hp_X]/1 mL; GOLD 8 [hp_X]/1 mL; BAPTISIA TINCTORIA ROOT 4 [hp_X]/1 mL; MERCURIC CYANIDE 8 [hp_X]/1 mL; CALOMEL 8 [hp_X]/1 mL; CORNUS RUGOSA WHOLE 9 [hp_X]/1 mL
INACTIVE INGREDIENTS: ALCOHOL; WATER

D-109

NDC 58264-0115-1

INDICATIONS

PURPOSE

Abscess at root of teeth.

INGREDIENTS

ACTIVE

Belladonna, 6x, 30x, Myristica sebifera 4x, 30x, Silicea 8x, 12x, Calcarea fluorica 8x, 12x, Borax 4x, 12x, Aurum metallicum 8x, 30x, Baptisia tinctoria 4x, 12x, Mercurius cyanatus 8x, 12x, Mercurius dulcis 8x, 12x, Cornus circinata 9x

INACTIVE

20% alcohol in purified water.

SUGGESTED DOSAGE

One dropper under tongue two times daily. Acute symptoms ½ dropper under tongue every 30 minutes for two hours.

STORAGE AND HANDLING

SHAKE WELL

Warnings

- Use only if cap seal is unbroken.

PREGNANCY OR BREAST FEEDING

- If pregnant or breastfeeding, ask a healthcare professional before use.

KEEP OUT OF REACH OF CHILDREN

- Keep this and all medication out of the reach of children.

To be used according to standard homeopathic indications.

PRINCIPAL DISPLAY PANEL - 1 FL. OZ. Bottle Label

DYNAMIC
NUTRITIONAL
ASSOCIATES, INC.

D 109

HOMEOPATHIC
STRESS FORMULA

1 FL. OZ.